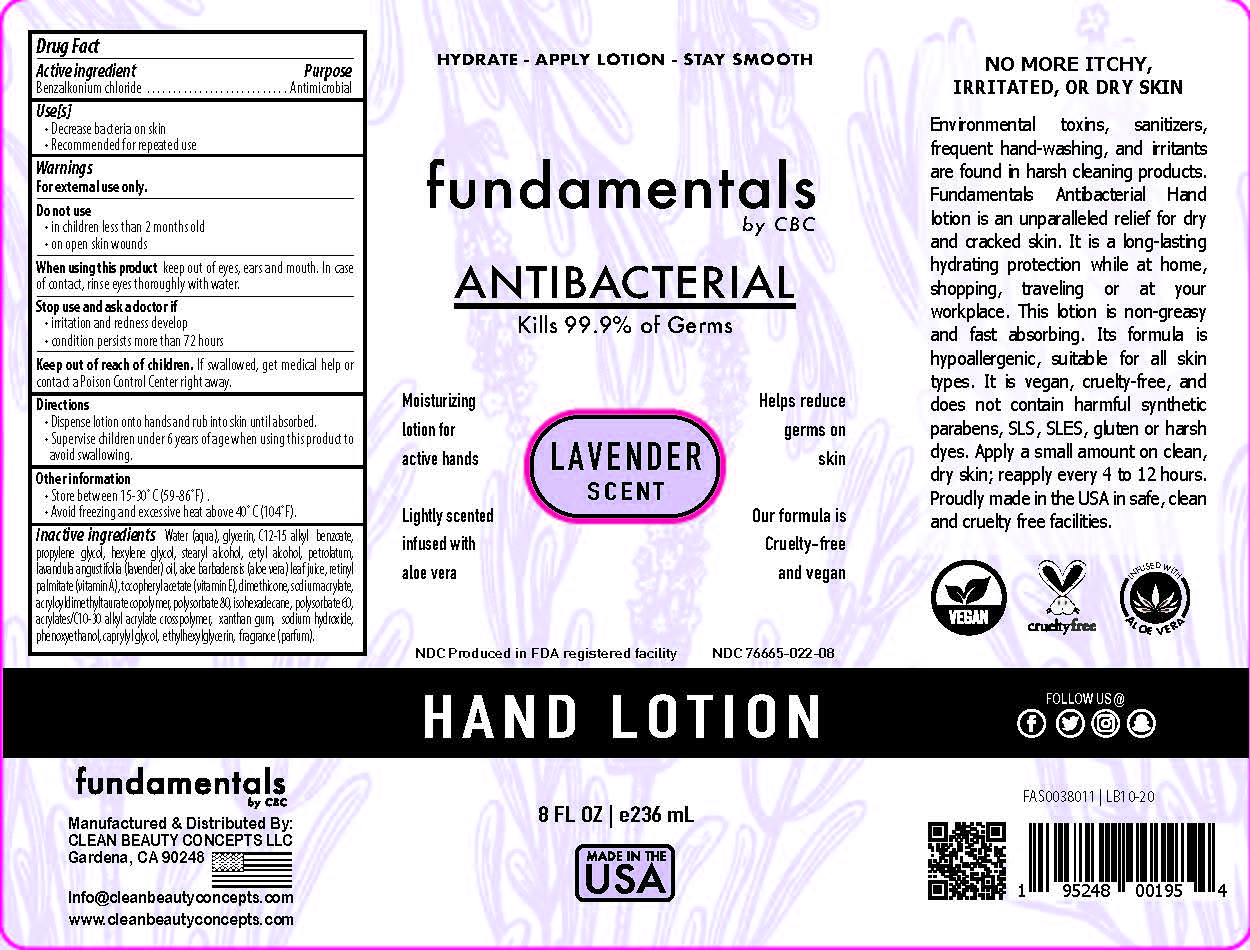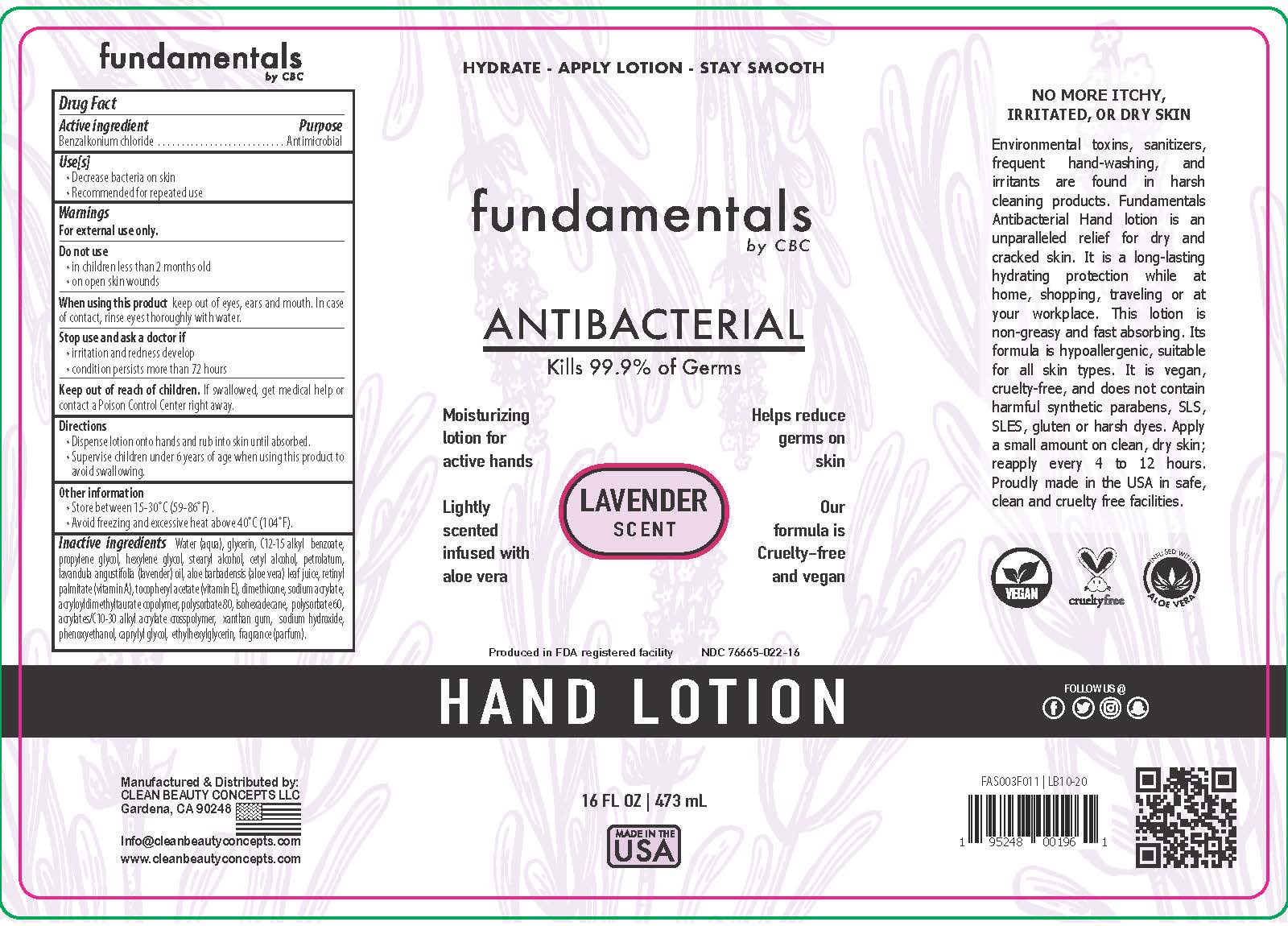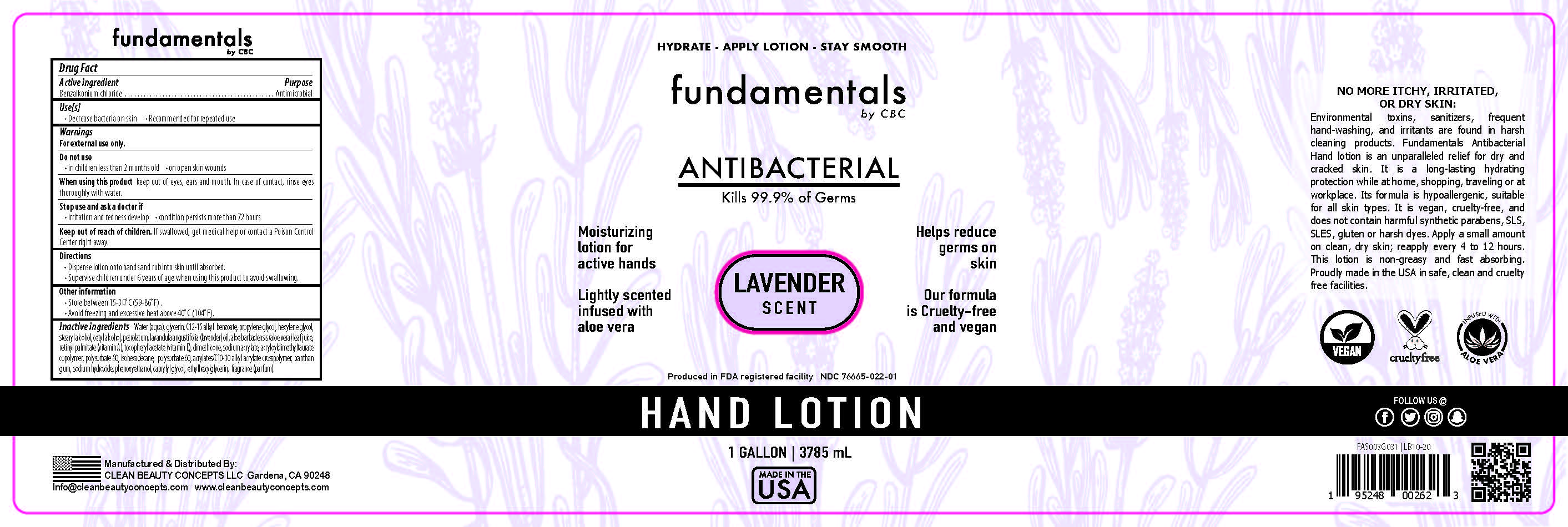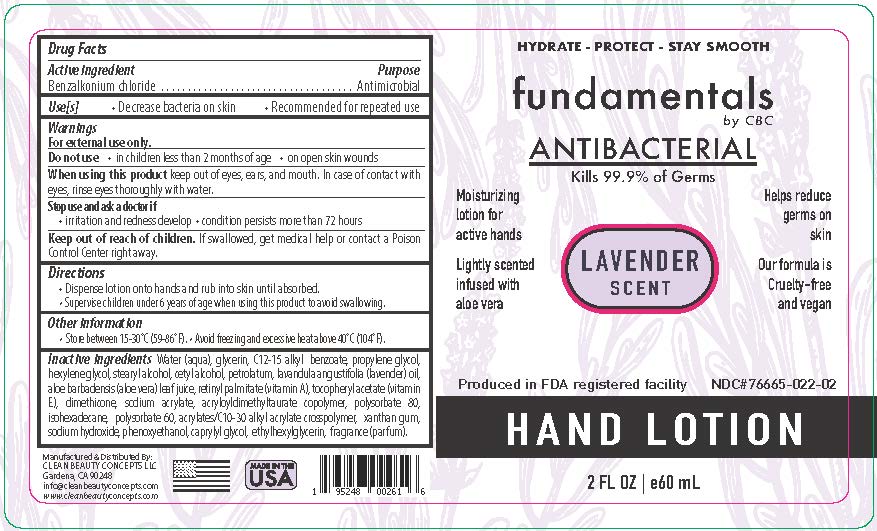 DRUG LABEL: Fundamentals Handlotion
NDC: 76665-022 | Form: LOTION
Manufacturer: Clean Beauty Concepts
Category: otc | Type: HUMAN OTC DRUG LABEL
Date: 20201226

ACTIVE INGREDIENTS: BENZALKONIUM CHLORIDE 0.13 mg/100 mL
INACTIVE INGREDIENTS: VITAMIN A PALMITATE 0.1 mL/100 mL; PHENOXYETHANOL 0.12 mL/100 mL; FRAGRANCE LAVENDER ORC1800979 0.1 mL/100 mL; WATER 78.273 mL/100 mL; PROPYLENE GLYCOL 3.15 mL/100 mL; PETROLATUM 1.9 mL/100 mL; GLYCERIN 4.85 mL/100 mL; ALOE VERA LEAF 0.15 mL/100 mL; DIMETHICONE 0.34 mL/100 mL; SODIUM ACRYLATE 0.14 mL/100 mL; SODIUM ACRYLATE/SODIUM ACRYLOYLDIMETHYLTAURATE COPOLYMER (4000000 MW) 0.145 mL/100 mL; POLYSORBATE 80 0.85 mL/100 mL; HEXYLENE GLYCOL 0.14 mL/100 mL; STEARYL ALCOHOL 2.145 mL/100 mL; CETYL ALCOHOL 1.852 mL/100 mL; LAVENDER OIL 0.125 mL/100 mL; .ALPHA.-TOCOPHEROL ACETATE 0.1 mL/100 mL; ISOHEXADECANE 0.47 mL/100 mL; POLYSORBATE 60 0.74 mL/100 mL; CARBOMER 1342 0.2 mL/100 mL; XANTHAN GUM 0.15 mL/100 mL; SODIUM HYDROXIDE 0.05 mL/100 mL; ETHYLHEXYLGLYCERIN 0.2 mL/100 mL; C12-20 ALKYL BENZOATE 3.44 mL/100 mL; CAPRYLYL GLYCOL 0.14 mL/100 mL

The hand lotion is manufactured using only the following United States Pharmacopoeia (USP) grade ingredients:

Benzalkonium chloride

Water (aqua)
Glycerin
C12-15 Alkyl benzoate
propylene glycol
stearyl alcohol
cetyl alcohol
Petrolatum
Lavendar oil
aloe barbadensis (aloe vera) leaf juice
retinyl palmitate (vitamin A)
tocopheryl acetate (vitamin E)
dimethicone
sodium acrylate
acryloyldimethyltaurate copolymer
polysorbate 80
isohexadecane
polysorbate 60
acrylates/C10 30 Alkyl acrylate crosspolymer
hexylene glycol
xanthan gum
sodium hydroxide
phenoxyethanol
caprylyl glycol
ethylhexylglycerin
fragrance (parfum)

Active Ingredient(s)

Benzalkonium chloride 0.13% v/v. Purpose: Antimicrobial

Purpose

Antimicrobial

Use

To decrease bacteria on skin

Recommended for repeat use

Warnings

For external use only.

When using this product keep out of eyes, ears, and mouth. In case of contact with eyes, rinse eyes thoroughly with water.

Stop use and ask a doctor if

irritation or redness develop

Condition persists more than 72 hours

Keep out of reach of children. If swallowed, get medical help or contact a Poison Control Center right away.

Directions

Dispense lotion onto hands and rub into skin until absorbed

Supervise children under 6 years of age when using this product to avoid swallowing

Other information

- Store between 15-30°C (59-86°F) .
  • Avoid freezing and excessive heat above 40°C (104°F).

Inactive ingredients

Water (aqua)

Glycerin

C12-15 Alkyl benzoate

propylene glycol

stearyl alcohol

cetyl alcohol

Petrolatum

Lavendar oil

aloe barbadensis (aloe vera) leaf juice

retinyl palmitate (vitamin A)

tocopheryl acetate (vitamin E)

dimethicone

sodium acrylate

acryloyldimethyltaurate copolymer

polysorbate 80

isohexadecane

polysorbate 60

acrylates/C10 30 Alkyl acrylate crosspolymer

hexylene glycol

xanthan gum

sodium hydroxide

phenoxyethanol

caprylyl glycol

ethylhexylglycerin

fragrance (parfum)

Do not Use

in children less than 2 months old

on open skin wounds

Package Label - Principal Display Panel

236 mL NDC: 76665-022-08

60 mL NDC: 76665-022-02

473 ml NDC: 76665-022-16

3785 ml NDC: 76665-022-01